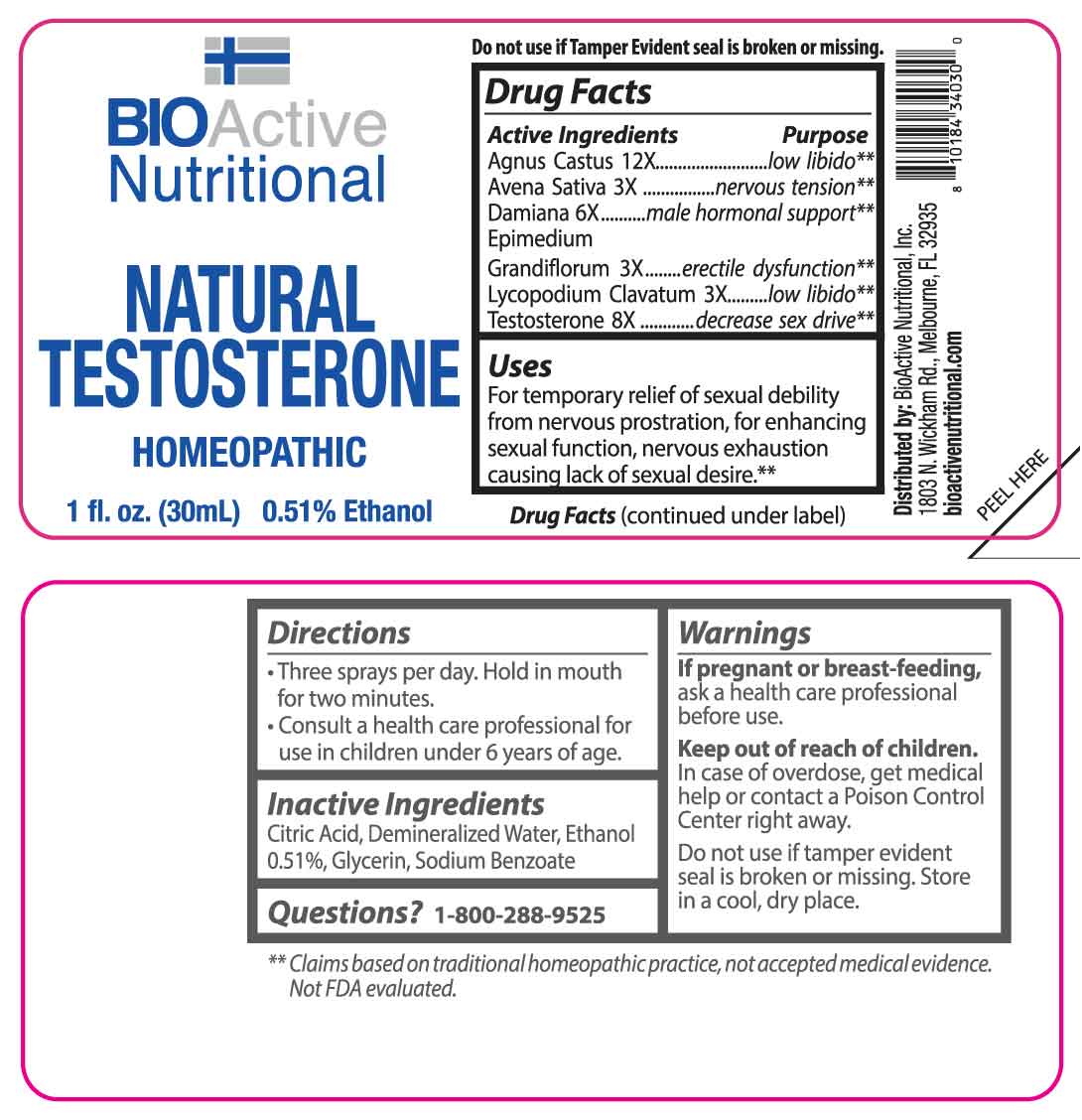 DRUG LABEL: Natural Testosterone
NDC: 43857-0268 | Form: SPRAY
Manufacturer: BioActive Nutritional, Inc.
Category: homeopathic | Type: HUMAN OTC DRUG LABEL
Date: 20250514
DEA Schedule: CIII

ACTIVE INGREDIENTS: AVENA SATIVA FLOWERING TOP 3 [hp_X]/1 mL; EPIMEDIUM GRANDIFLORUM TOP 3 [hp_X]/1 mL; LYCOPODIUM CLAVATUM SPORE 3 [hp_X]/1 mL; TURNERA DIFFUSA LEAFY TWIG 6 [hp_X]/1 mL; TESTOSTERONE 8 [hp_X]/1 mL; CHASTE TREE 12 [hp_X]/1 mL
INACTIVE INGREDIENTS: CITRIC ACID MONOHYDRATE; GLYCERIN; SODIUM BENZOATE; WATER; ALCOHOL

DRUG FACTS:

ACTIVE INGREDIENTS:

Agnus Castus 12X, Avena Sativa 3X, Damiana 6X, Epimedium Grandiflorum 3X, Lycopodium Clavatum 3X, Testosterone 8X.

PURPOSE:

Agnus Castus – low libido,** Avena Sativa – nervous tension,** Damiana – male hormonal support,** Epimedium Grandiflorum – erectile dysfunction,** Lycopodium Clavatum – low libido,** Testosterone – decrease sex drive**

**Claims based on traditional homeopathic practice, not accepted medical evidence. Not FDA evaluated.

USES:

For temporary relief of sexual debility from nervous prostration, for enhancing sexual function, nervous exhaustion causing lack of sexual desire.**

**Claims based on traditional homeopathic practice, not accepted medical evidence. Not FDA evaluated.

WARNINGS:

If pregnant or breast-feeding, ask a health care professional before use.

Keep out of reach of children. In case of overdose, get medical help or contact a Poison Control Center right away.

Do not use if tamper evident seal is broken or missing.

Store in a cool, dry place.

KEEP OUT OF REACH OF CHILDREN:

In case of overdose, get medical help or contact a Poison Control Center right away.

DIRECTIONS:

• Three sprays per day. Hold in mouth for two minutes.

• Consult a health care professional for use in children under 6 years of age.

INACTIVE INGREDIENTS:

Citric Acid, Demineralized Water, Ethanol 0.51%, Glycerin, Sodium Benzoate.

QUESTIONS:

Distributed by:

BioActive Nutritional, Inc.

1803 N. Wickham Rd.

Melbourne, FL 32935

bioactivenutritional.com

1-800-288-9525

PACKAGE LABEL DISPLAY:

BIOActive Nutritional

NATURAL

TESTOSTERONE

HOMEOPATHIC

1 FL OZ (30 ml)